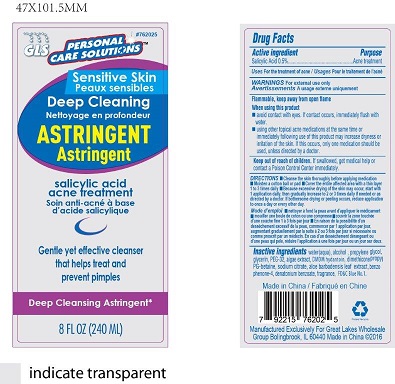 DRUG LABEL: Acne
NDC: 64092-325 | Form: LIQUID
Manufacturer: Great Lakes Wholesale, Marketing and Sales Inc
Category: otc | Type: HUMAN OTC DRUG LABEL
Date: 20160830

ACTIVE INGREDIENTS: SALICYLIC ACID 1.2 g/240 mL
INACTIVE INGREDIENTS: WATER

DESCRIPTION

GLW PERSONAL CARE SOLUTIONS

Deep Cleaning Astringent

Sensitive Skin

Salicylic Acid acne treatment

Gentle yet effective cleanser that helps treat and prevent pimples.

8 FL OZ (240 mL)

Active Ingedient Purpose

Salicylic Acid 0.5%...............................................................Acne treatment

PURPOSE

Deep Cleaning acne treatment

INDICATIONS AND USAGE

For treatment of acne

WARNINGS

For external use only.

Flammable, keep away from open flame

When using this product, avoid contact with eyes. If contact occurs, immediately flush with water.

Using other topical acne medications at the same time or immediately following use of this product may increase dryness of irritation of the skin. If this occurs, only one medication should be used, unless directed by a doctor.c

KEEP OUT OF REACH OF CHILDREN

If swallowed, get medical help or contact a Poison Control Center immediately.

DOSAGE AND ADMINISTRATION

Topical sensitive skin cleaning solution

0.5% Salicylic Acid

INSTRUCTIONS FOR USE

- Cleanse the skin thoroughly before applying medication
- Moisten a cotton ball or pad
- Cover the entire affected area with a thin layer 1 to 3 times daily
- Because excessive drying of the skin may occur, start with 1 application daily, then gradually increase to 2 or 3 times daily if needed or as directed by a doctor..
- If bothersome drying or peeling occurs, reduce application to once a day or every other day.

INACTIVE INGREDIENT

water (aqua), alcohol, propylene glycol, glycerin, PEG-32, algae extract, DMDM hydantion, dimethicone propyl PG-betaine, sodium citrate, aloe barbadensis leaf exract, benzophenone-4, denatonium benzoate, fragrance, FD&C Blue No. 1.